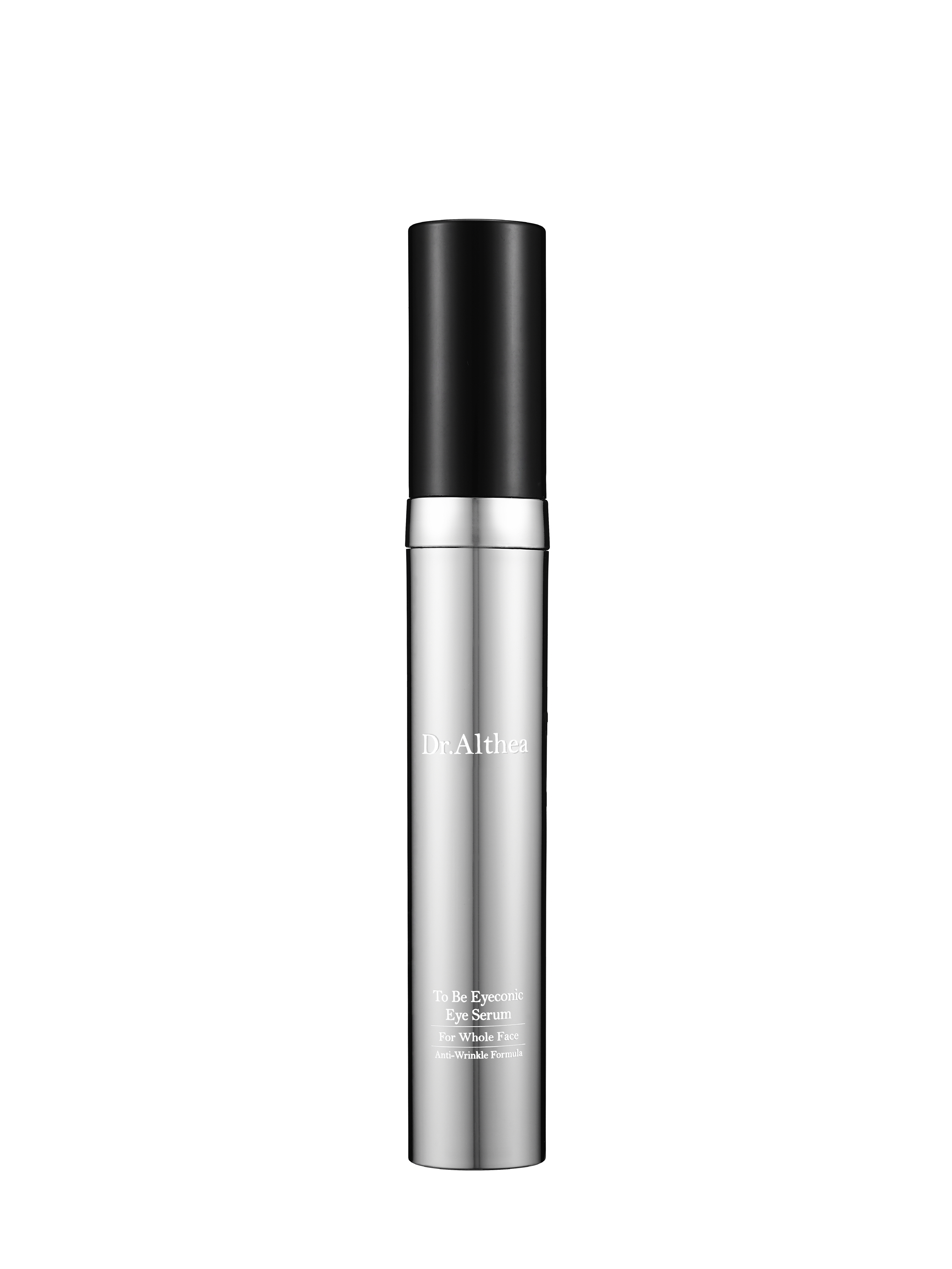 DRUG LABEL: Dr.Althea To Be Eyeconic Eye Serum
NDC: 70905-0010 | Form: CREAM
Manufacturer: Dr. Althea
Category: otc | Type: HUMAN OTC DRUG LABEL
Date: 20161011

ACTIVE INGREDIENTS: DIMETHICONE 6.0192 g/100 mL
INACTIVE INGREDIENTS: WATER; BUTYLENE GLYCOL

Drug Facts

ACTIVE INGREDIENT

DIMETHICONE

INACTIVE INGREDIENT

WATER, CYCLOPENTASILOXANE, BUTYLENE GLYCOL, GLYCERIN, TOCOPHEROL, ETC.

PURPOSE

Skin Protectant

keep out of reach of the children

INDICATIONS AND USAGE

Take appropriate amount of eye serum evenly spread on the skin

WARNINGS

1. If the following symptoms occur after product use, stop using the product immediately and consult a dermatologist (continuous use can exacerbate the symptoms).
1) Occurrence of red spots, swelling, itchiness, and other skin irritation
2) If the symptoms above occur after the application area is exposed to direct sunlight
2. Do not use on open wounds, eczema, and other skin irritations
3. Precaution for Storage and Handling
1) Close the lid after use
2) Keep out of reach of infants and children
3) Do not to store in a place with high/low temperature and exposed to direct sunlight

DOSAGE AND ADMINISTRATION

for external use only